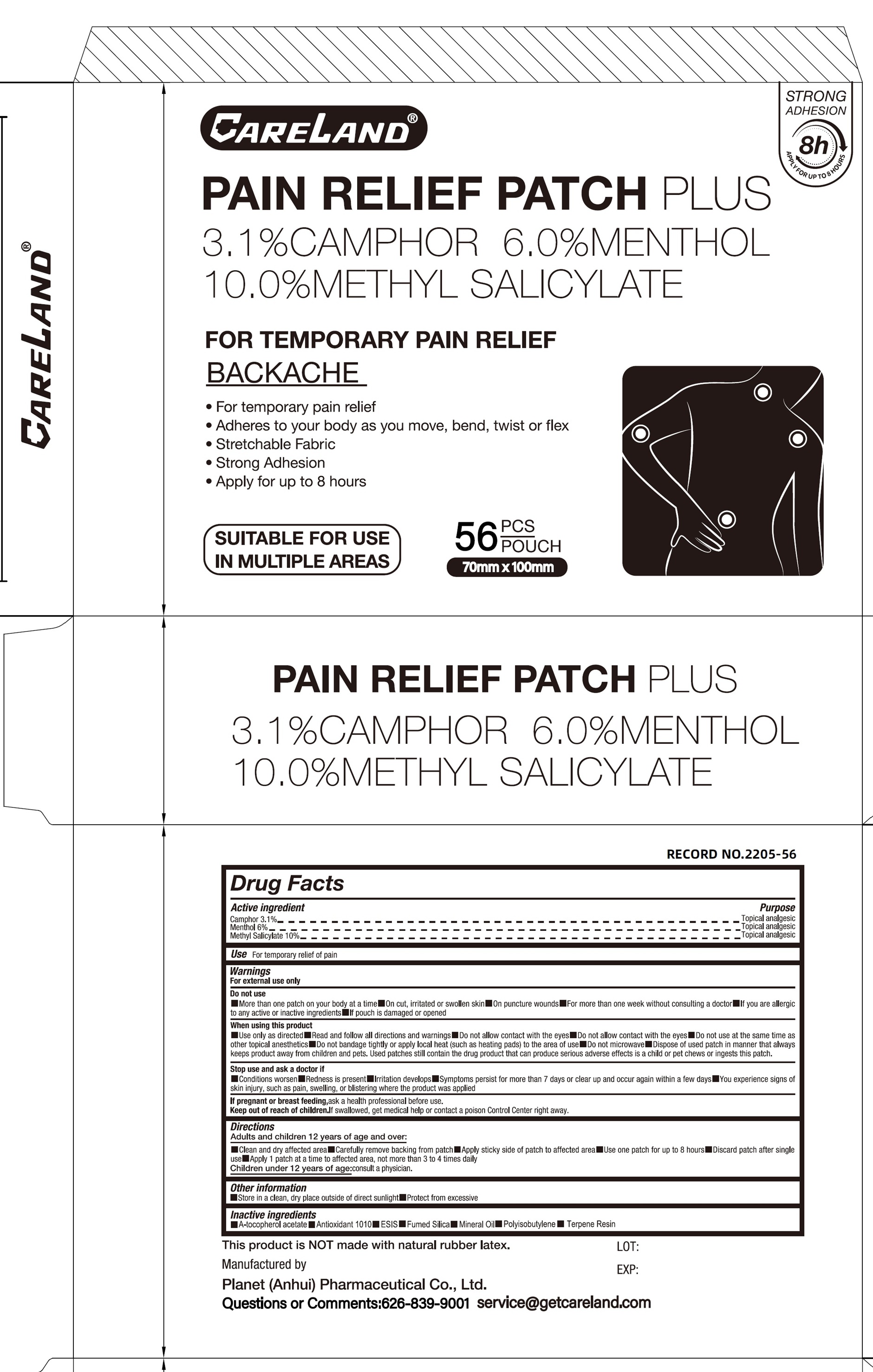 DRUG LABEL: Careland Pain Relief Plus
NDC: 75568-039 | Form: PATCH
Manufacturer: Planet (Anhui) Pharmaceutical Co., Ltd.
Category: otc | Type: HUMAN OTC DRUG LABEL
Date: 20251212

ACTIVE INGREDIENTS: CAMPHOR (SYNTHETIC) 31 mg/1 g; MENTHOL 60 mg/1 g; METHYL SALICYLATE 100 mg/1 g
INACTIVE INGREDIENTS: PENTAERYTHRITOL TETRAKIS(3-(3,5-DI-TERT-BUTYL-4-HYDROXYPHENYL)PROPIONATE); MINERAL OIL; TERPENE RESIN

Careland Pain Relief Patch Plus

Active Ingredients

Camphor 3.1%

Menthol 6.0%

Methyl Salicylate 10.0%

Purpose

Topical analgesic

Use

For temporary relifeof pain

Warnings

For external use only

Do not use

- More than one patch on your body at a time
- On cut, irritated or swollen skin
- On puncture wounds
- For more than one week without consulting a doctor
- If you are allergic to any active or inactive ingredients
- If pouch is damaged or opened

When using this product

- Use only as directed
- Read all follow all directions and warnings
- Do not allow contact with the eyes
- do not allow contact with the eyes
- Do not use at the same time as other topical anesthetics
- Do not bandage tightly or apply local heat (such as heating pads) to the area of use
- Do not microwave
- Dispose of used patch in manner that always keeps product away from children and pets, Used patches still contain the drug product that can produce serious adverse effects is a child or pet chews or ingests this patch.

Stop use and ask a doctor if

- Conditions wrosen
- Redness is present
- Irritation develops
- Symptoms persist for more than 7 days or clear up and occur again within a few days
- You experience signs of skin injury, such as pain swelling, or blistering where the product was applied

If pregnant or breast feeding,

ask a health professional before use.

Keep out of reach of children.

If swallowed, get medical help or contact a poison Control Center right away.

Directons

Adults and children 12 years of age and over:

- Clean and dry affected area
- Carefully remove backing from patch
- Apply sticky side of patch to affected area
- Use one patch for up to 8 hours
- Discard patch after single use
- Apply 1 patch at a time to affected area, not more than 3 to 4 times daily

Children under 12 years of age: consult a physician.

Other information

- Store in clean, dry place outside of direct sunlight
- Protect from excessive

Inactive ingredients

- • A-tocopherol acetate • Antioxidant 1010 • ESIS • Fumed Silica • Mineral Oil • Polyisobutylene • Terpene Resin